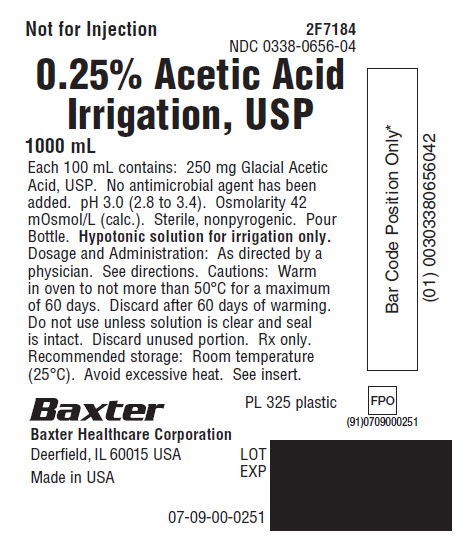 DRUG LABEL: Acetic Acid
NDC: 0338-0656 | Form: IRRIGANT
Manufacturer: Baxter Healthcare Corporation
Category: prescription | Type: HUMAN PRESCRIPTION DRUG LABEL
Date: 20180202

ACTIVE INGREDIENTS: ACETIC ACID 250 mg/100 mL
INACTIVE INGREDIENTS: WATER

0.25% Acetic Acid Irrigation, USP
in Plastic Pour Bottle

DESCRIPTION

0.25% Acetic Acid Irrigation, USP, is a sterile, nonpyrogenic hypotonic solution for irrigation of the urinary bladder. Each 100 mL contains 250 mg Glacial Acetic Acid, USP, (CH3COOH) in Water for Injection, USP. pH 3.0 (2.8 to 3.4). Osmolarity: 42 mOsmol/L (calc.). No antimicrobial agent has been added.

The container is made from specially formulated polyolefin (PL 325). The polyolefin is a copolymer of ethylene and propylene. It contains no plasticizers or other mobile additives. As a result, the container has virtually no extractability or leachability. The total extractables after two years of storage being less than 0.01 ppm. It is also relatively impermeable to water vapor transmission and, therefore, requires no vapor barrier to maintain the proper drug concentration.

CLINICAL PHARMACOLOGY

The minimal amount of acetic acid which may enter the systemic circulation is readily metabolized.

INDICATIONS AND USAGE

0.25% Acetic Acid Irrigation, USP, is indicated as a constant or intermittent bladder rinse to help prevent the growth and proliferation of susceptible urinary pathogens (especially ammonia forming bacteria) in the management of patients who require prolonged placement of an indwelling urethral catheter. It also may be used for periodic irrigation of an indwelling catheter to help maintain patency by reducing the formation of calcium encrustations.

CONTRAINDICATIONS

None known

WARNINGS

Not for injection.

Use of this solution in patients with mucosal lesions of the urinary bladder may be harmful due to irritation of the lesion. Absorption via open lesions of the bladder mucosa may result in systemic acidosis.

The contents of an opened container should be used promptly to minimize the possibility of bacterial growth or pyrogen formation. Discard the unused portion of irrigating solution since no antimicrobial agent has been added.

PRECAUTIONS

Pregnancy

Teratogenic Effects

Animal reproduction studies have not been conducted with 0.25% Acetic Acid Irrigation, USP. It is also not known whether 0.25% Acetic Acid Irrigation, USP can cause fetal harm when administered to a pregnant woman or can affect reproduction capacity. 0.25% Acetic Acid Irrigation, USP should be given to a pregnant woman only if clearly needed.

Pediatric Use

Safety and effectiveness in pediatric patients have not been established.

Warm in oven to not more than 50°C for a maximum of 60 days. Discard after 60 days of warming.

Do not administer unless the solution is clear and the seal is intact.

ADVERSE REACTIONS

Systemic acidosis, pain and hematuria have been reported in patients receiving urinary bladder irrigation with 0.25% Acetic Acid Irrigation, USP.

Should adverse reactions occur, discontinue the irrigation and reevaluate the clinical status of the patient.

DOSAGE AND ADMINISTRATION

The volume of solution needed will vary with nature and duration of the urologic procedure, according to physician’s instructions.

Irrigation drug products should be inspected visually for particulate matter and discoloration prior to administration whenever solution and container permit.

HOW SUPPLIED

0.25% Acetic Acid Irrigation, USP is supplied in a plastic pour bottle as follows:

2F7184 | 1000 mL | NDC 0338-0656-04

Exposure of pharmaceutical products to heat should be minimized. Avoid excessive heat. It is recommended that the product be stored at room temperature (25°C): brief exposure up to 40ºC does not adversely affect the product.

Baxter Healthcare Corporation
Deerfield, IL 60015 USA

Printed in USA

Baxter is a registered trademark of Baxter International Inc.

07-19-00-0228

Rev. February 2018

PACKAGE LABEL - PRINCIPAL DISPLAY PANEL

Container Label

Not for Injection 2F7184
NDC 0338-0656-04

0.25% Acetic Acid
Irrigation, USP

1000 mL

Each 100 mL contains: 250 mg Glacial Acetic
Acid, USP. No antimicrobial agent has been
added. pH 3.0 (2.8 to 3.4). Osmolarity 42
mOsmol/L (calc.). Sterile, nonpyrogenic. Pour
Bottle. Hypotonic solution for irrigation only.
Dosage and Administration: As directed by a
physician. See directions. Cautions: Warm
in oven to not more than 50°C for a maximum
of 60 days. Discard after 60 days of warming.
Do not use unless solution is clear and seal
is intact. Discard unused portion. Rx only.
Recommended storage: Room temperature
(25°C). Avoid excessive heat. See insert.

PL 325 plastic

Baxter Logo
Baxter Healthcare Corporation
Deerfield, IL 60015 USA

Made in USA

LOT
EXP

07-09-00-0251

FPO
(91)0709000251
Bar Code

Bar Code Posit ion Only*
(01) 00303380656042